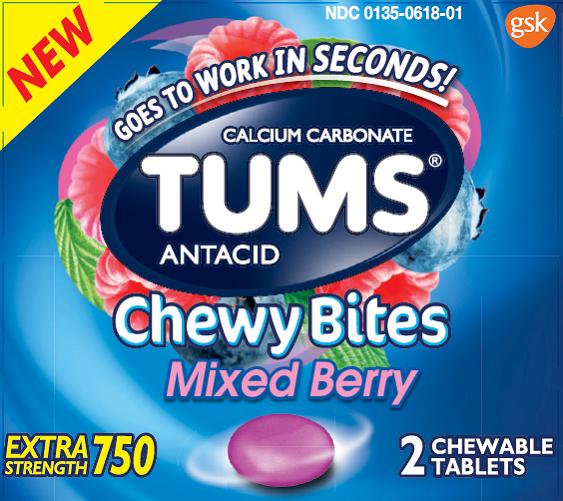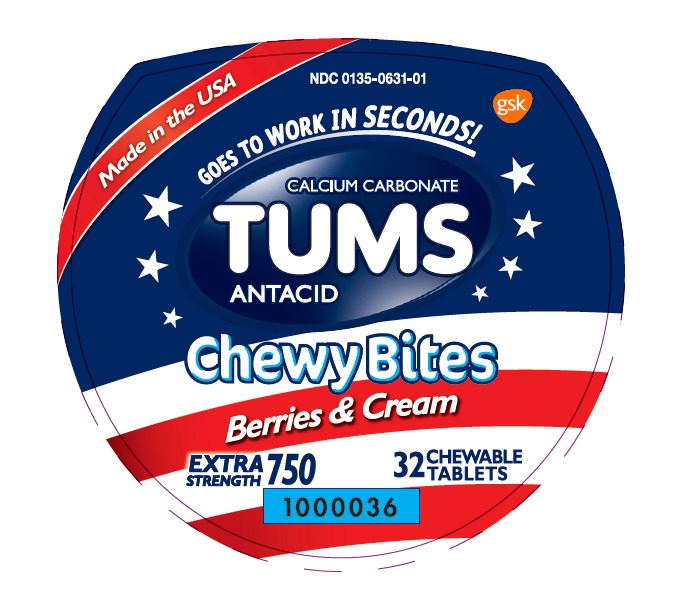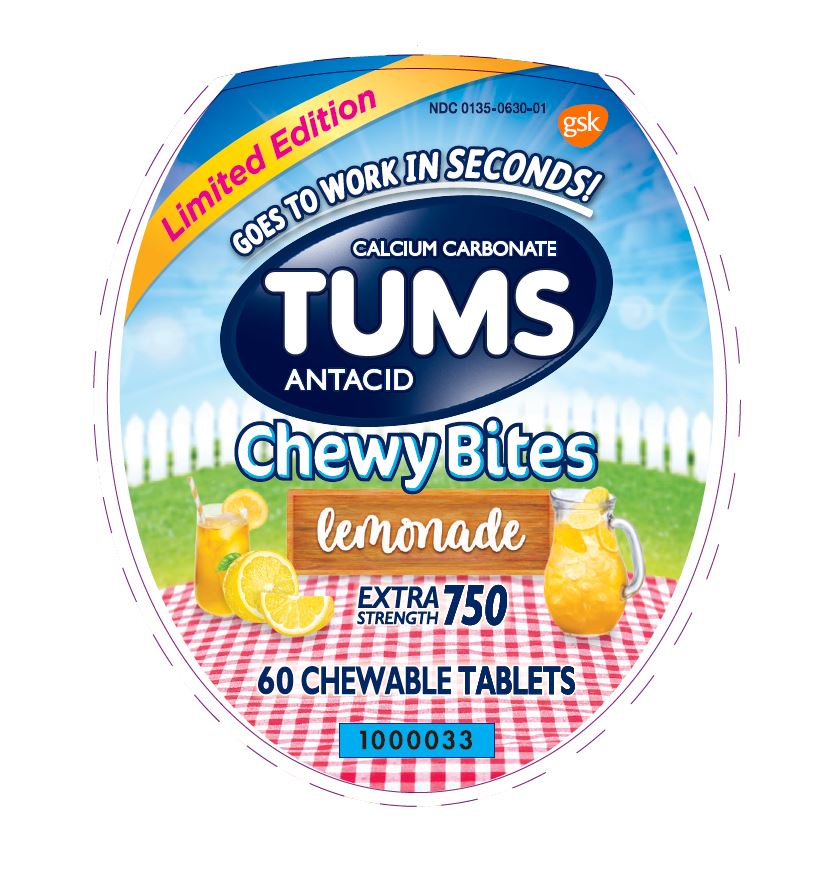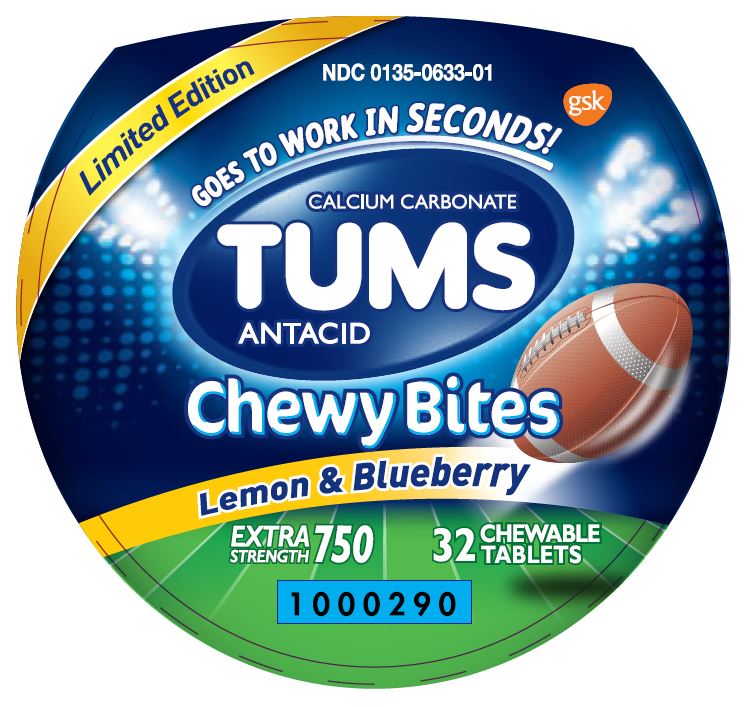 DRUG LABEL: Tums Chewy Bites
NDC: 0135-0618 | Form: TABLET, CHEWABLE
Manufacturer: Haleon US Holdings LLC
Category: otc | Type: HUMAN OTC DRUG LABEL
Date: 20240302

ACTIVE INGREDIENTS: CALCIUM CARBONATE 750 mg/1 1
INACTIVE INGREDIENTS: ACACIA; ALCOHOL; AMMONIA; YELLOW WAX; CARMINIC ACID; CARNAUBA WAX; CITRIC ACID MONOHYDRATE; COCONUT OIL; STARCH, CORN; CORN SYRUP; ICODEXTRIN; ETHYL ACETATE; FD&C BLUE NO. 1; ALUMINUM OXIDE; FD&C BLUE NO. 2; FD&C RED NO. 40; FD&C YELLOW NO. 6; ISOPROPYL ALCOHOL; MALTODEXTRIN; METHYLPARABEN; BUTYL ALCOHOL; PHOSPHORIC ACID; PROPYLPARABEN; PROPYLENE GLYCOL; WATER; SHELLAC; SORBIC ACID; SORBITOL; SOYBEAN OIL; LECITHIN, SOYBEAN; SUCROSE; TERT-BUTYLHYDROQUINONE; TITANIUM DIOXIDE; CORN OIL

Drug Facts

Active ingredient (per tablet)

Calcium Carbonate USP 750mg

Purpose

Antacid

Uses

relieves

- heartburn
- acid indigestion
- sour stomach
- upset stomach associated with these symptoms

Warnings

Ask a doctor or pharmacist before use if you are

presently taking a prescription drug. Antacids may interact with certain prescription drugs.

When using this product

- do not take more than 6 tablets in 24 hours
- if pregnant do not take more than 6 tablets in 24 hours
- do not use the maximum dosage for more than 2 weeks except under the advice and supervision of a doctor

Directions

- adults and children 12 years of age and over:chew 2-4 tablets as symptoms occur, or as directed by a doctor
- do not take for symptoms that persist for more than 2 weeks unless advised by a doctor

Other Information

- each chewable tablet contains:elemental calcium 300mg
- do not store above 25°C (77°F)

Inactive ingredients (Mixed Berry)

Acacia gum, alcohol, ammonium hydroxide, beeswax, carmine, carnauba wax, citric acid, coconut oil, corn starch, corn syrup, dextrin, ethyl acetate, ethyl alcohol, FD&C blue #1 alum lake, FD&C blue #2 alum lake, FD&C red #40 alum lake, FD&C yellow #6 alum lake, flavors, gum arabic, isopropyl alcohol, maltodextrin, methylparaben, n-butyl alcohol, phosphoric acid, propylparaben, propylene glycol, purified water, shellac, sorbic acid, sorbitol, soybean oil, soy lecithin, sucrose, TBHQ, titanium dioxide, vegetable oil

Inactive Ingredients (Berries & Cream)

alcohol, ammonium hydroxide, beeswax, carnauba wax, citric acid, coconut oil, corn starch, corn syrup, dextrin, ethyl acetate, FD&C blue no.1 aluminum lake, FD&C red no. 40, FD&C red no. 40 aluminum lake, FD&C yellow no. 5 aluminum lake (tartrazine), FD&C yellow no. 6 aluminum lake, flavors, gum arabic, isopropyl alcohol, lecithin, maltodextrin, medium chain triglycerides, methylparaben, modified starch, n-butyl alcohol, phosphoric acid, propylene glycol, propylparaben, purified water, shellac, sodium benzoate, sorbic acid, sorbitol, soybean oil, sucrose, tert-butylhydroquinone, titanium dioxide, vegetable oil

Inactive Ingredients (Lemonade)

alcohol, ammonium hydroxide, beeswax, carnauba wax, citric acid, coconut oil, corn starch, corn syrup, dextrin, DL-alpha tocopherol, ethyl acetate, FD&C blue no.1 aluminum lake, FD&C blue no.2 aluminum lake, FD&C red no. 40 aluminum lake, FD&C yellow no. 5 aluminum lake (tartrazine), FD&C yellow no. 6 aluminum lake, flavors, gum arabic, isopropyl alcohol, lecithin, maltodextrin, medium chain triglycerides, methylparaben, modified starch, n-butyl alcohol, phosphoric acid, propylene glycol, propylparaben, purified water, shellac, sodium benzoate, sorbic acid, sorbitol, soybean oil, sucrose, tert-butylhydroquinone, titanium dioxide, vegetable oil

Inactive Ingredients (Lemon & Blueberry)

alcohol, ammonium hydroxide, beeswax, carnauba wax, citric acid, coconut oil, corn starch, corn syrup, dextrin, ethyl acetate, FD&C blue no.1 aluminum lake, FD&C red no. 40 aluminum lake, FD&C yellow no. 5 aluminum lake (tartrazine), FD&C yellow no. 6 aluminum lake, flavors, gum arabic, isopropyl alcohol, lecithin, maltodextrin, medium chain triglycerides, methylparaben, modified starch, n-butyl alcohol, phosphoric acid, propylene glycol, propylparaben, purified water, shellac, sorbic acid, sorbitol, soybean oil, sucrose, tert-butylhydroquinone, titanium dioxide, vegetable oil

Questions?

Call 1-800-897-7535

Principal Display Panel

NDC 0135-0618-01

TUMS®

CALCIUM CARBONATE

ANTACID

Chewy Bites

Mixed Berry

NEW

GOES TO WORK IN SECONDS!

EXTRA STRENGTH 750

2 CHEWABLE TABLETS

Safety sealed : Do not use if packet is damaged or open.

Distributed by:

GSKConsumer Healthcare

Warren, NJ 07059

Trademarks are owned by or licensed to the GSK group of companies.

©2016 GSK or its licensor

105902XA

Principal Display Panel

NDC 0135-0631-01

TUMS

CALCIUM CARBONATE

ANTACID

Chewy Bites

Berries & Cream

Made in the USA

GOES TO WORK IN SECONDS!

EXTRA STRENGTH 750

32 CHEWABLE TABLETS

Do not use if printed inner safety seal under cap is broken or missing.

Distributed by: GSKConsumer Healthcare

Warren, NJ 07059

Trademarks are owned by or licensed to the GSK group of companies.

©2018 GSK or its licensor.

1000037

Principal Display Panel

NDC 0135-0630-01

TUMS

CALCIUM CARBONATE

ANTACID

Chewy Bites

lemonade

Limited Edition

GOES TO WORK IN SECONDS!

EXTRA STRENGTH 750

60 CHEWABLE TABLETS

Do not use if printed inner safety seal under cap is broken or missing.

Distributed by: GSKConsumer Healthcare

Warren, NJ 07059

Trademarks are owned by or licensed to the GSK group of companies.

©2018 GSK or its licensor.

1000034

Principal Display Panel

NDC 0135-0633-01

TUMS

CALCIUM CARBONATE

ANTACID

Chewy Bites

Lemon & Blueberry

Limited Edition

GOES TO WORK IN SECONDS!

EXTRA STRENGTH 750

32 CHEWABLE TABLETS

Do not use if printed inner safety seal under cap is broken or missing.

Distributed by: GSKConsumer Healthcare

Warren, NJ 07059

Trademarks are owned by or licensed to the GSK group of companies.

©2019 GSK or its licensor.

1000290